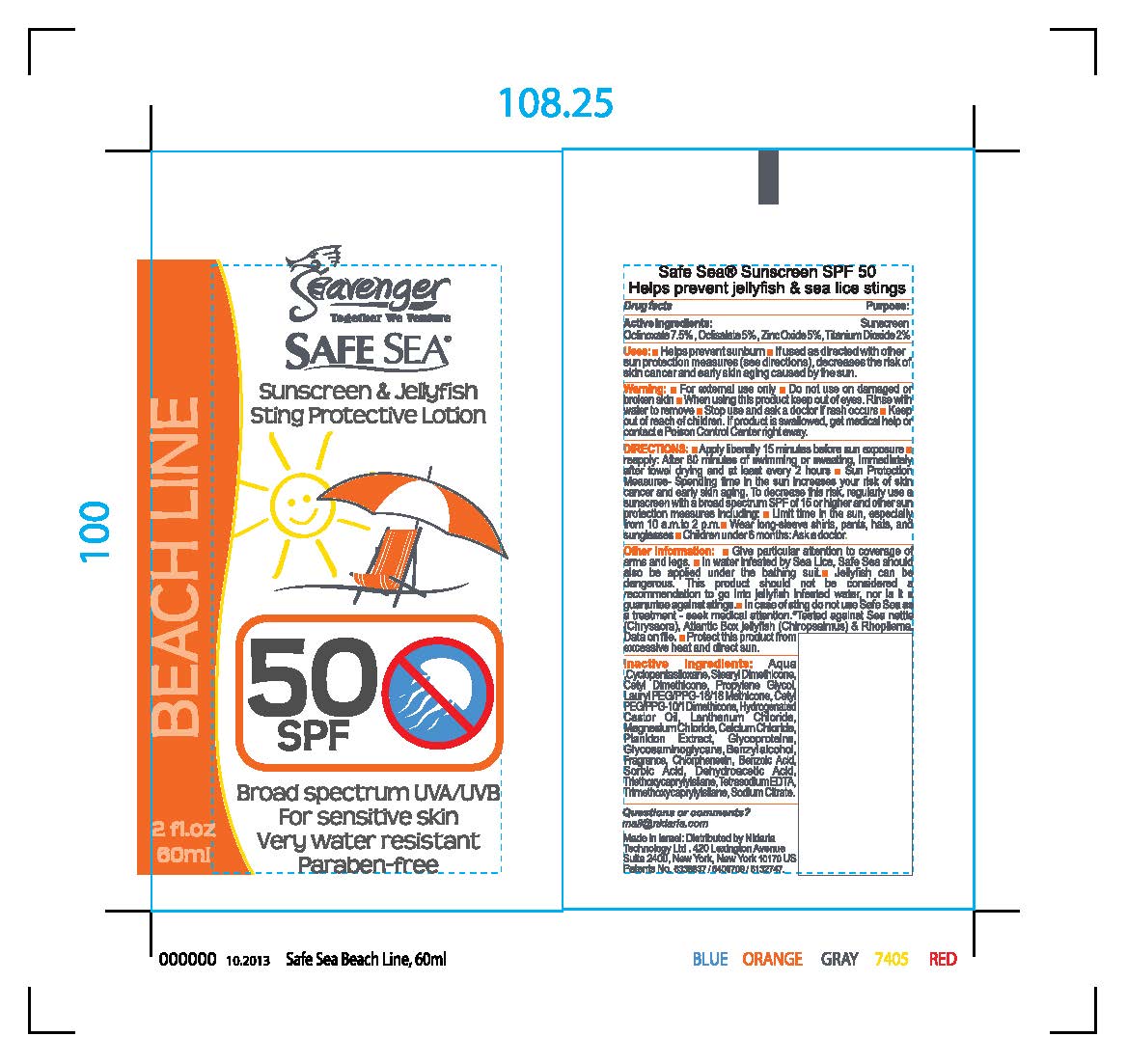 DRUG LABEL: Safe Sea SPF 60
NDC: 66134-060 | Form: LOTION
Manufacturer: SASA Cosmetics
Category: otc | Type: HUMAN OTC DRUG LABEL
Date: 20160315

ACTIVE INGREDIENTS: OCTINOXATE 75 mg/1 g; OCTISALATE 50 mg/1 g; ZINC OXIDE 50 mg/1 g; TITANIUM DIOXIDE 20 mg/1 g
INACTIVE INGREDIENTS: WATER; CYCLOMETHICONE 5; STEARYL DIMETHICONE (400 MPA.S AT 50C); CETYL DIMETHICONE 25; PROPYLENE GLYCOL; LAURYL PEG/PPG-18/18 METHICONE; CETYL PEG/PPG-10/1 DIMETHICONE (HLB 2); HYDROGENATED CASTOR OIL; PANTHENOL; .ALPHA.-TOCOPHEROL ACETATE; LANTHANUM CHLORIDE; MAGNESIUM CHLORIDE; CALCIUM CHLORIDE; PHAEODACTYLUM TRICORNUTUM; SACCHAROMYCES CEREVISIAE; POLYSULFATED GLYCOSAMINOGLYCAN; BENZYL ALCOHOL; CHLORPHENESIN; BENZOIC ACID; SORBIC ACID; DEHYDROACETIC ACID; EDETATE SODIUM; SODIUM CITRATE; TRIETHOXYCAPRYLYLSILANE; TRIMETHOXYCAPRYLYLSILANE

Drug Facts

INACTIVE INGREDIENT

Inactive Ingredients: Aqua, Cyclopentasiloxane, Stearyl Dimethicone, Cetyl Dimethicone,

Propylene Glycol, Lauryl PEG / PPG - 18/18 Methicone, Cetyl PEG/PPG-10/1 Dimethicone,

Hydrogenated Castor Oil, Panthenol, Tocopheryl Acetate, Lanthanum Chloride,

Magnesium Chloride, Calcium Chloride, Plankton Extract, Glycoproteins, Glycosaminoglycans,

Benzyl Alcohol, Fragrance, Chlorphenesin, Benzoic Acid, Sorbic Acid, Dehydroacetic Acid,

Tetrasodium EDTA, Sodium Citrate, Triethoxycaprylylsilane, Trimethoxycaprylylsilane

Active Ingredients:

Octinoxate 7.5 %

Octisalate 5 %

Zinc Oxide 5 %

Titanium Dioxide 2 %

Purpose:

Sunscreen

INDICATIONS AND USAGE

Uses: Helps prevent sunburn -- If used as directed with other sun

protection measures (see directions), decreases the risk of skin cancer

and early skin aging caused by the sun

WARNINGS

Warning: -For external use only -- Do not use on damaged or broken skin

--When using this product keep out of eyes. Rinse with water to

remove -- Stop sue and ask a doctor if rash occurs--Keep out of reach

of children -- If product is swallowed, get medical help or contact a Poison

Control Center right away.

DOSAGE AND ADMINISTRATION

DIRECTIONS: Apply liberally 15 minutes before sun exposure --

reapply. After 80 minutes of swimming or sweating, immediately after towel

drying and at least every 2 hours -- Sun Protection Measures-Spending time in the

sun increases your risk of skin cancer and early skin aging. To

decrease this risk, regularly use a sunscreen with a broad spectrum SPF of

15 or higher and other sun protection measures including: - Limit time

in the sun, especially from 10 a.m. to 2 p.m. -- Wear long-sleeve shirts, pants,

hats, and sunglasses -- Children under 6 months: Ask a doctor.

Keep out of reach of children. If product is swallowed, get medical help or

contact a Poison Control Center right away.

Other Information: Give particular attention to coverage of arms

and legs. - In water infested by Sea Lice, Safe Sea should also be applied under the

bathing suit. - Jellyfish can be dangerous. This product should not be considered a

recommendation to go into jellyfish infested water, nor is it

a guarantee against stings. - In case of sting do not use Safe Sea

as a treatment - seek medical attention.

Tested against Sea nettle (Chrysaora) Atlantic Box jellyfish (Chiropsalmus)

and Rhopilema. Data on file. - Protect this product form excessive heat

and direct sunlight